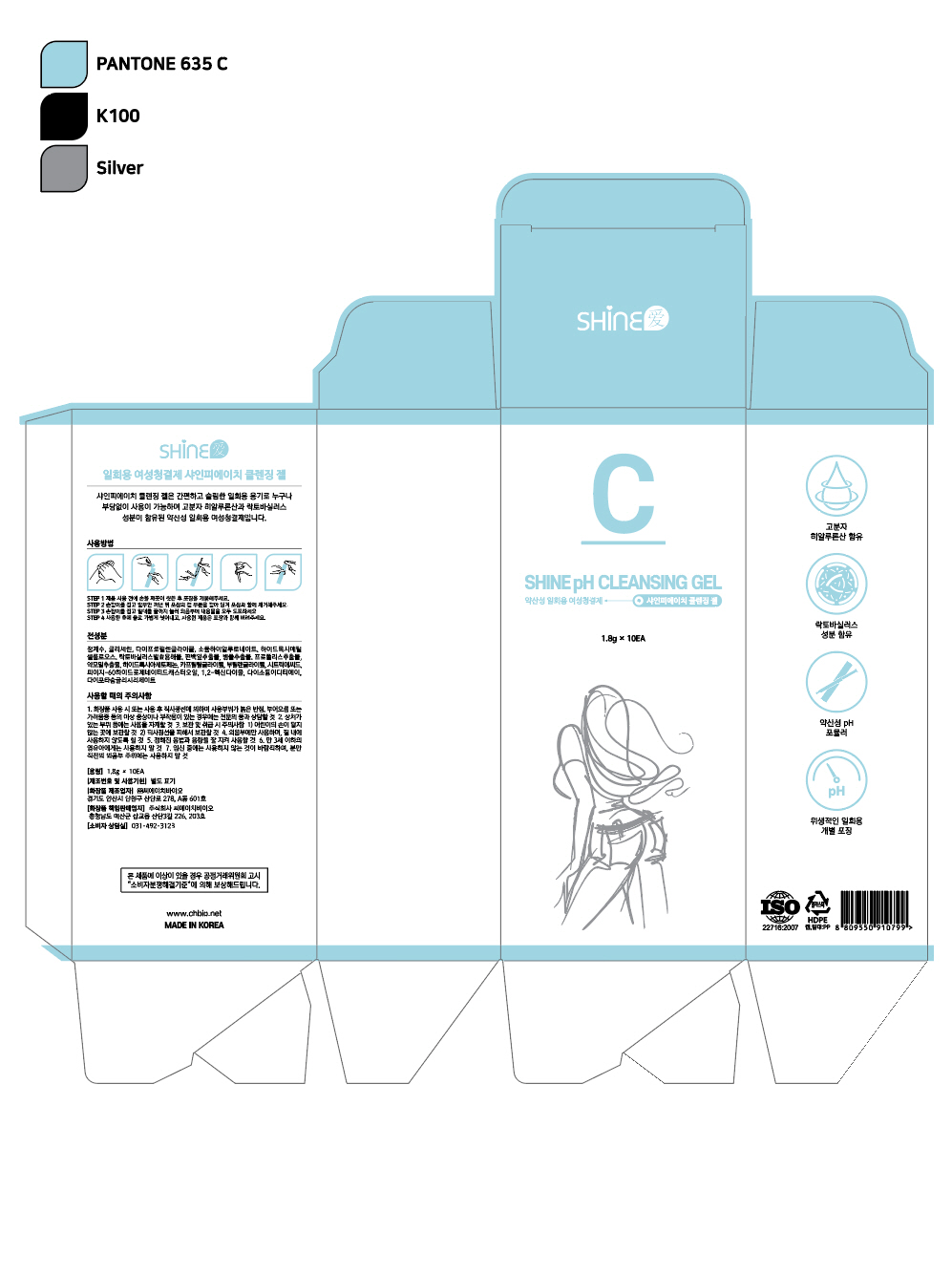 DRUG LABEL: SHINE pH CLEANSING
NDC: 73305-0011 | Form: GEL
Manufacturer: CH BIO CO., LTD.
Category: otc | Type: HUMAN OTC DRUG LABEL
Date: 20250226

ACTIVE INGREDIENTS: SODIUM HYALURONATE 0.5 g/100 g
INACTIVE INGREDIENTS: WATER; GLYCERIN; CENTELLA ASIATICA LEAF

ACTIVE INGREDIENT

Sodium Hyaluronate

INACTIVE INGREDIENT

Water
Glycerin
Dipropylene Glycol
Hydroxyethylcellulose
Lactobacillus Ferment Lysate
Chamaecyparis Obtusa Leaf Extract
Centella Asiatica Extract
Propolis Extract
Houttuynia Cordata Extract
Hydroxyacetophenone
Caprylyl Glycol
Butylene Glycol
Citric Acid
PEG-60 Hydrogenated Castor Oil
1,2-Hexanediol
Disodium EDTA
Dipotassium Glycyrrhizate

PURPOSE

feminine hygiene

keep out or reach of the children

INDICATIONS AND USAGE

Step 1

Wash your hands thoroughly before opening the product packaging.

Step 2

Hold the handle and partially remove the product. Then pull on the cap portion of the packaging to remove it along with the packaging.

Step 3

Holding the handle, press the plunger all the way down to apply the entire contents to the vulva.

Step 4

After use, gently rinse with water. Dispose of the used product along with its packaging.

WARNINGS

Precautions for Use

If you experience abnormal symptoms or side effects such as red spots, swelling, or itching on the area of use during or after using the cosmetic product due to direct sunlight, consult with a specialist.

Avoid using on areas with wounds.

Precautions for storage and handling:

Keep out of reach of children.

Store away from direct sunlight.

Use only on the vulva, do not use inside the vagina.

Follow the prescribed usage and dosage carefully.

Do not use on infants and toddlers under 3 years old.

It is advisable not to use during pregnancy, and do not use on the area around the vulva immediately before delivery.

DOSAGE AND ADMINISTRATION

for external use only